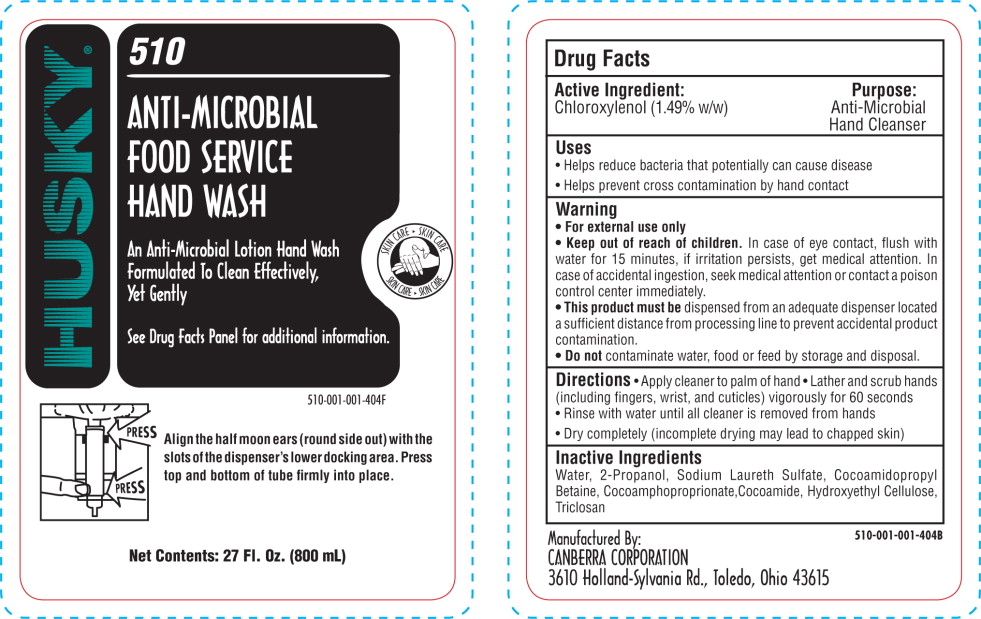 DRUG LABEL: HUSKY 510 Anti-Microbial Food Service Hand Cleaner
NDC: 63779-510 | Form: LIQUID
Manufacturer: Canberra Corporation
Category: otc | Type: HUMAN OTC DRUG LABEL
Date: 20100511

ACTIVE INGREDIENTS: chloroxylenol 15.75 g/1000 mL
INACTIVE INGREDIENTS: water; sodium laureth sulfate; cocamidopropyl betaine; hydroxyethyl cellulose (2000 CPS at 1%); isopropyl alcohol; coco diethanolamide; triclosan

HUSKY®
510
ANTI-MICROBIAL
FOOD SERVICE
HAND WASH

Active Ingredient:

Chloroxylenol (1.49% w/w)

Purpose:

Antiseptic Hand Sanitizer

Uses

- Helps reduce bacteria that potentially can cause disease
- Helps prevent cross contamination by hand contact

KEEP OUT OF REACH OF CHILDREN

- For external use only
- Keep out of reach of children. In case of eye contact flush with water for 15 minutes, if irritation persists, get medical attention. In case of accidental ingestion, seek medical attention or contact a poison control center immediately.
- This product must be dispensed from an adequate dispenser located a sufficient distance from processing line to prevent accidental product contamination.
- Do not contaminate water, food or feed by storage and disposal.

Directions

- Apply cleaner to palm of hand
- Lather and scrub hands (including fingers, wrist, and cuticles) vigorously for 60 seconds
- Rinse with water until all cleaner is removed from hands
- Dry completely (incomplete drying may lead to chapped skin).

Inactive Ingredients

Water, 2-Propanol, Sodium Laureth Sulfate, Cocoamidopropyl Betaine, Cocoamphoproprionate, Cocoamide, Hydroxyethyl Cellulose, Triclosan

Principal Display Panel – Bag Label

HUSKY®

510

ANTI-MICROBIAL

FOOD SERVICE

HAND WASH

An Anti-Microbial Lotion Hand Wash Formulated To Clean Effectively, Yet Gently

See Drug Facts panel for additional information.

Align the half moon ears (round side out) with the slots of the dispenser's lower docking area. Press top and bottom of tube firmly into place.